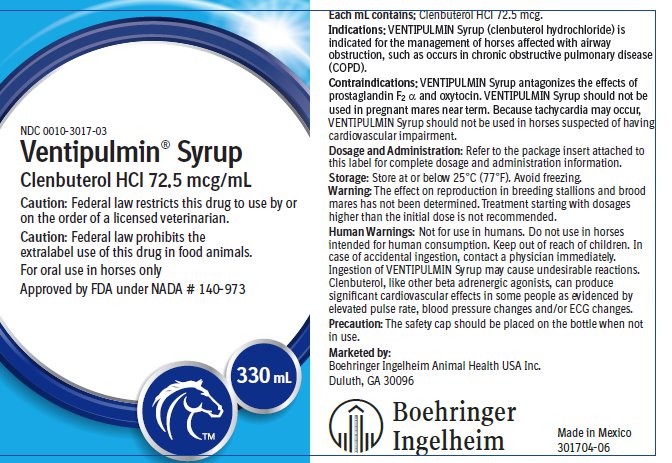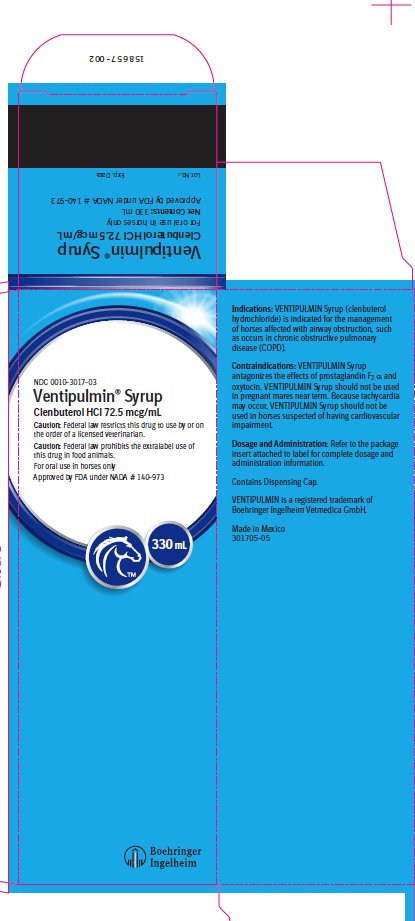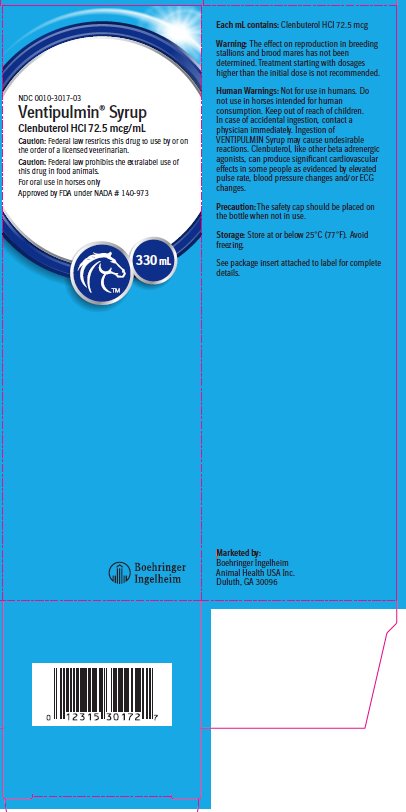 DRUG LABEL: Ventipulmin
NDC: 0010-3017 | Form: SYRUP
Manufacturer: Boehringer Ingelheim Animal Health USA Inc.
Category: animal | Type: PRESCRIPTION ANIMAL DRUG LABEL
Date: 20220608

ACTIVE INGREDIENTS: CLENBUTEROL HYDROCHLORIDE 0.0725 mg/1 mL

Ventipulmin® Syrup
(clenbuterol HCl)

Approved by FDA under NADA # 140-973

For oral use in horses only

Caution:

Federal law restricts this drug to use by or on the order of a licensed veterinarian.

Caution:

Federal law prohibits the extralabel use of this drug in food animals.

Each mL contains:

Clenbuterol HCl 72.5 mcg

Description:

Clenbuterol (4-amino-alpha-[(tert-butylamino) methyl]-3, 5-dichlorobenzyl alcohol hydrochloride) is a beta-2-adrenergic agonist which provides bronchodilating properties as well as other effects, with minimum effect on the cardiovascular system. It is provided as a colorless, palatable syrup. VENTIPULMIN Syrup (clenbuterol hydrochloride) is antagonized by beta-adrenergic blocking agents.

Indications:

VENTIPULMIN Syrup (clenbuterol hydrochloride) is indicated for the management of horses affected with airway obstruction, such as occurs in chronic obstructive pulmonary disease (COPD).

Contraindications:

VENTIPULMIN Syrup antagonizes the effects of prostaglandin F2 α and oxytocin. VENTIPULMIN Syrup should not be used in pregnant mares near term. Because tachycardia may occur, VENTIPULMIN Syrup should not be used in horses suspected of having cardiovascular impairment.

Warning:

The effect on reproduction in breeding stallions and brood mares has not been determined. Treatment starting with dosages higher than the initial dose is not recommended.

Human Warnings:

Not for use in humans. Do not use in horses intended for human consumption. Keep out of reach of children. In case of accidental ingestion, contact a physician immediately. Ingestion of VENTIPULMIN Syrup may cause undesirable reactions. Clenbuterol, like other beta adrenergic agonists, can produce significant cardiovascular effects in some people as evidenced by elevated pulse rate, blood pressure changes and/or ECG changes.

Dosage and Administration:

Administer orally twice a day (b.i.d.). Initial dose is 0.5 mL/100 lbs body weight (0.8 mcg/kg) twice daily.

Dosage Schedule:

Initial dosage: administer 0.5 mL/100 lbs (0.8 mcg/kg) for 3 days (6 treatments); If no improvement, administer 1.0 mL/100 lbs (1.6 mcg/kg) for 3 days (6 treatments); If no improvement, administer 1.5 mL/100 lbs (2.4 mcg/kg) for 3 days (6 treatments); If no improvement, administer 2.0 mL/100 lbs (3.2 mcg/kg) for 3 days (6 treatments); If no improvement, horse is non-responsive to clenbuterol and treatment should be discontinued. Recommended duration of treatment at effective dose is 30 days. At the end of this 30-day treatment period, drug should be withdrawn to determine recurrence of signs. If signs return, the 30-day treatment regimen may be repeated. If repeating treatment, the step-wise dosage schedule should be repeated.

Directions for Administration:

Remove safety cap and seal; replace with enclosed plastic dispensing cap. Remove cover from dispensing tip and connect syringe (without needle). Draw out appropriate volume of VENTIPULMIN Syrup. Administer orally to the horse. Replace cover on dispensing tip to prevent leakage.

Dosage Calculation Chart

Lbs. Body; Weight | mL/treatment; at 0.5 mL/100#; (0.8 mcg/kg) | mL/treatment; at 1.0 mL/100#; (1.6 mcg/kg) | mL/treatment; at 1.5 mL/100#; (2.4 mcg/kg) | mL/treatment; at 2.0 mL/100#; (3.2 mcg/kg)
500; 600; 700; 800; 900; 1000; 1100; 1200; 1300; 1400; 1500; 1600; 1700; 1800 | 2.5; 3.0; 3.5; 4.0; 4.5; 5.0; 5.5; 6.0; 6.5; 7.0; 7.5; 8.0; 8.5; 9.0 | 5.0; 6.0; 7.0; 8.0; 9.0; 10.0; 11.0; 12.0; 13.0; 14.0; 15.0; 16.0; 17.0; 18.0 | 7.5; 9.0; 10.5; 12.0; 13.5; 15.0; 16.5; 18.0; 19.5; 21.0; 22.5; 24.0; 25.5; 27.0 | 10.0; 12.0; 14.0; 16.0; 18.0; 20.0; 22.0; 24.0; 26.0; 28.0; 30.0; 32.0; 34.0; 36.0

Administer two treatments per day.

Precaution:

The safety cap should be placed on the bottle when not in use.

Adverse Reactions:

Mild sweating, muscle tremor, restlessness, urticaria and tachycardia may be observed in some horses during the first few days of treatment. May cause elevated creatine kinase (CK) serum levels. Ataxia was observed in 3 out of 239 horses (1.3%) in clinical studies. To report suspected adverse events, for technical assistance, or to obtain a copy of the Safety Data Sheet (SDS), contact Boehringer Ingelheim Animal Health USA Inc. at 1-888-637-4251. For additional information about adverse drug experience reporting for animal drugs, contact FDA at 1-888-FDA-VETS or online at www.fda.gov/reportanimalae.

How Supplied:

VENTIPULMIN Syrup is available in 100 mL and 330 mL plastic bottles containing 72.5 mcg clenbuterol HCl per mL.

NDC 0010-3017-02 – 100 mL, NDC 0010-3017-03 – 330 mL

Storage:

Store at or below 25°C (77°F). Avoid freezing.

VENTIPULMIN is a registered trademark of Boehringer Ingelheim Vetmedica GmbH.

Marketed by:

Boehringer Ingelheim Animal Health USA Inc.

Duluth, GA 30096

Principal Display Panel – 330 mL Container Label

NDC 0010-3017-03

Ventipulmin® Syrup

Clenbuterol HCl 72.5 mcg/mL

Caution: Federal law restricts this drug to use by or on the order of a licensed veterinarian.

Caution: Federal law prohibits the extralabel use of this drug in food animals.

For oral use in horses only

Approved by FDA under NADA # 140-973

Principal Display Panel – 330 mL Display Carton – Front and Side Panel

NDC 0010-3017-03

Ventipulmin® Syrup

Clenbuterol HCl 72.5 mcg/mL

Caution: Federal law restricts this drug to use by or on the order of a licensed veterinarian.

Caution: Federal law prohibits the extralabel use of this drug in food animals.

For oral use in horses only

Approved by FDA under NADA # 140-973